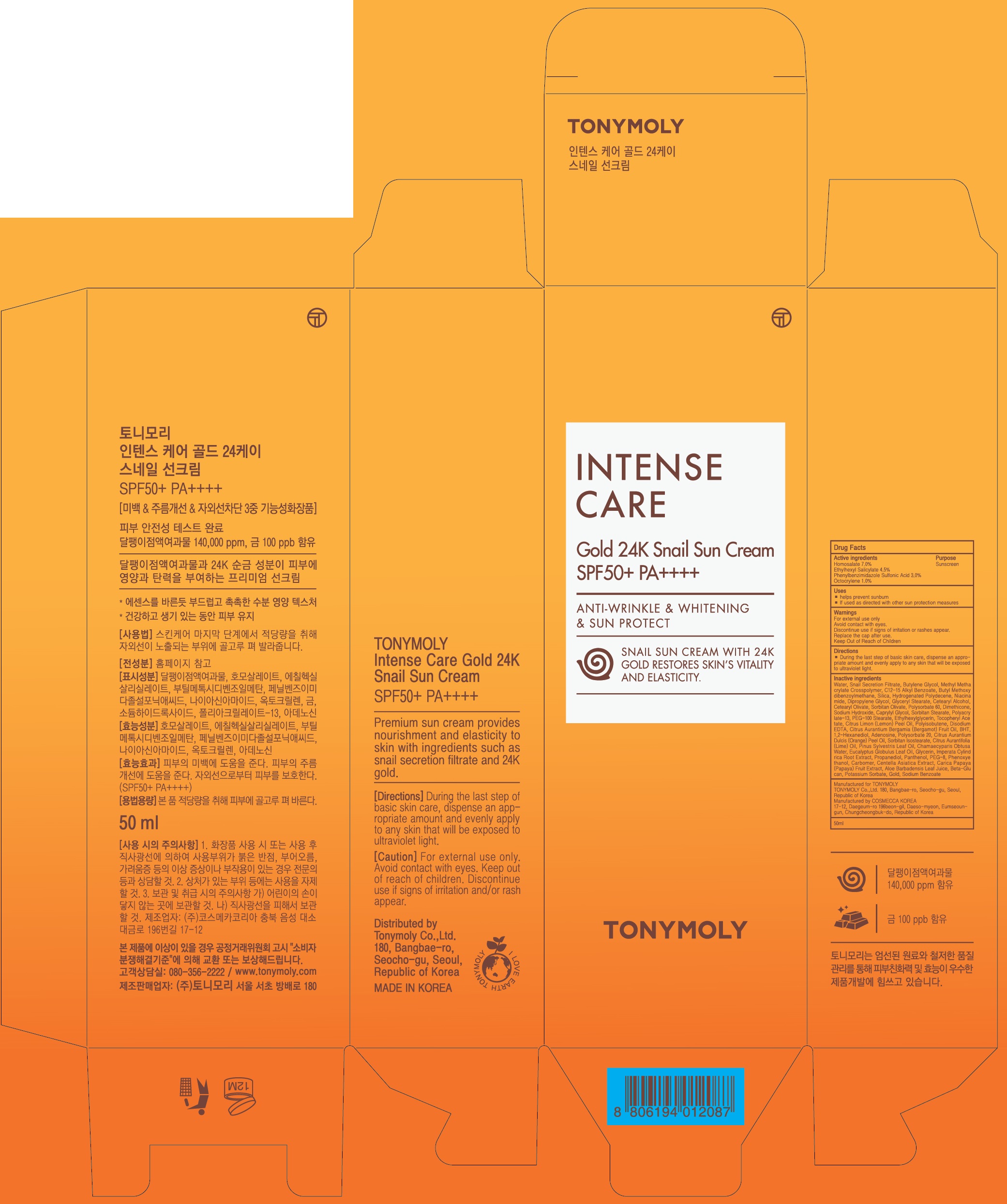 DRUG LABEL: INTENSE CARE GOLD 24K SNAIL SUN
NDC: 59078-325 | Form: CREAM
Manufacturer: TONYMOLY CO.,LTD
Category: otc | Type: HUMAN OTC DRUG LABEL
Date: 20170831

ACTIVE INGREDIENTS: Homosalate 3.50 g/50 mL; Octisalate 2.25 g/50 mL; Ensulizole 1.50 g/50 mL; Octocrylene 0.50 g/50 mL
INACTIVE INGREDIENTS: Water; Butylene Glycol

ACTIVE INGREDIENT

Active ingredients: Homosalate 7.0%, Ethylhexyl Salicylate 4.5%, Phenylbenzimidazole Sulfonic Acid 3.0%, Octocrylene 1.0%

INACTIVE INGREDIENT

Inactive ingredients: Water, Snail Secretion Filtrate, Butylene Glycol, Methyl Methacrylate Crosspolymer, C12-15 Alkyl Benzoate, Butyl Methoxydibenzoylmethane, Silica, Hydrogenated Polydecene, Niacinamide, Dipropylene Glycol, Glyceryl Stearate, Cetearyl Alcohol, Cetearyl Olivate, Sorbitan Olivate, Polysorbate 60, Dimethicone, Sodium Hydroxide, Caprylyl Glycol, Sorbitan Stearate, Polyacrylate-13, PEG-100 Stearate, Ethylhexylglycerin, Tocopheryl Acetate, Citrus Limon (Lemon) Peel Oil, Polyisobutene, Disodium EDTA, Citrus Aurantium Bergamia (Bergamot) Fruit Oil, BHT, 1,2-Hexanediol, Adenosine, Polysorbate 20, Citrus Aurantium Dulcis (Orange) Peel Oil, Sorbitan Isostearate, Citrus Aurantifolia (Lime) Oil, Pinus Sylvestris Leaf Oil, Chamaecyparis Obtusa Water, Eucalyptus Globulus Leaf Oil, Glycerin, Imperata Cylindrica Root Extract, Propanediol, Panthenol, PEG-8, Phenoxyethanol, Carbomer, Centella Asiatica Extract, Carica Papaya (Papaya) Fruit Extract, Aloe Barbadensis Leaf Juice, Beta-Glucan, Potassium Sorbate, Gold, Sodium Benzoate

PURPOSE

Purpose: Sunscreen

WARNINGS

Warnings: For external use only Avoid contact with eyes. Discontinue use if signs of irritation or rashes appear. Replace the cap after use. Keep Out of Reach of Children

DESCRIPTION

Uses: - Helps prevent sunburn - If used as directed with other sun protection measures

Directions: During the last step of basic skin care, dispense an appropriate amount and evenly apply to any skin that will be exposed to ultraviolet light.